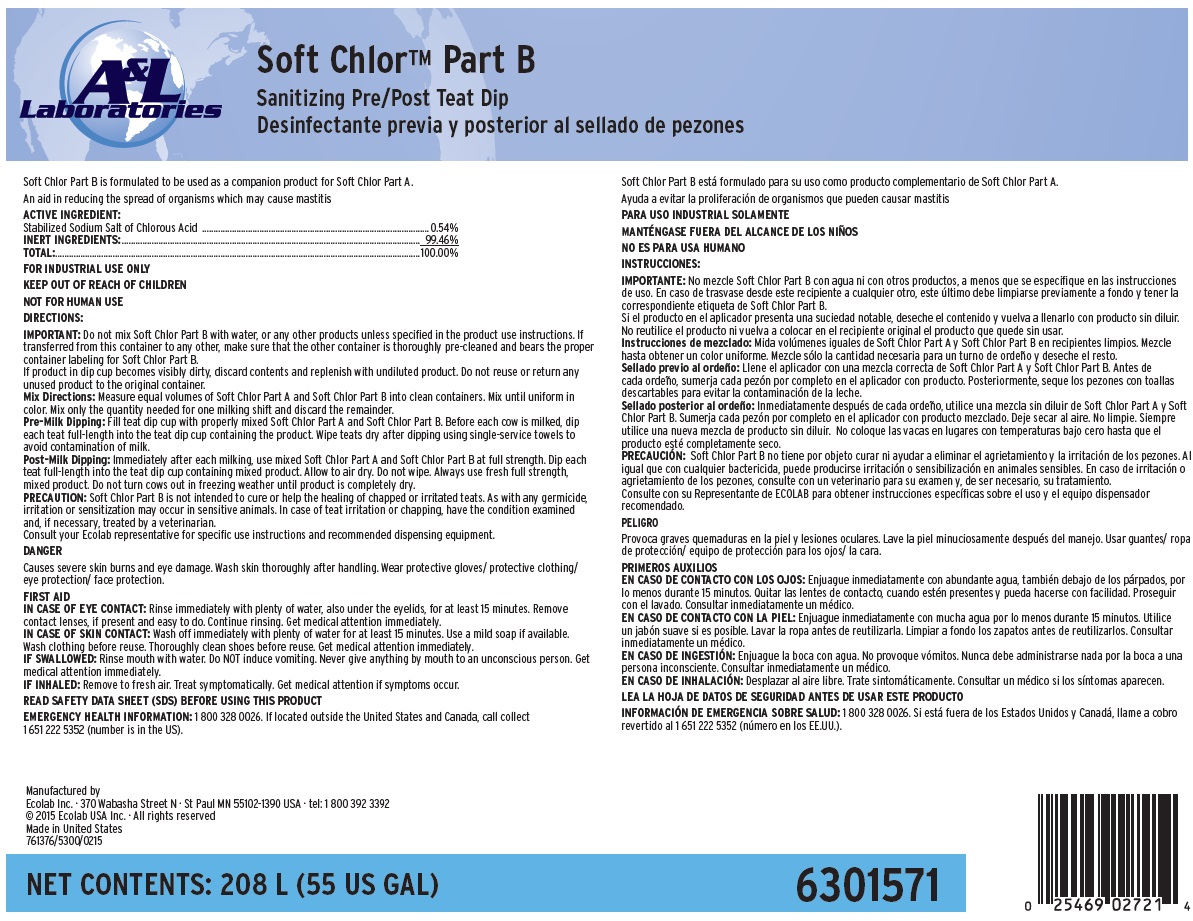 DRUG LABEL: Soft Chlor Part B
NDC: 47593-606 | Form: SOLUTION
Manufacturer: Ecolab Inc.
Category: animal | Type: OTC ANIMAL DRUG LABEL
Date: 20251116

ACTIVE INGREDIENTS: SODIUM CHLORITE 5.4 1/1 mL
INACTIVE INGREDIENTS: WATER

SAFE HANDLING WARNING

Soft Chlor Part B is formulated to be used as a companion product for Soft Chlor Part A.

FOR INDUSTRIAL USE ONLY

KEEP OUT OF REACH OF CHILDREN

NOT FOR HUMAN USE

DANGER

Causes severe skin burns and eye damage. Wash skin thoroughly after handling. Wear protective gloves/ protective clothing/ eye protection/ face protection.

DIRECTIONS:

IMPORTANT: Do not mix Soft Chlor Part B with water, or any other products unless specified in the product use instructions. If transferred from this container to any other, make sure that the other container is thoroughly pre-cleaned and bears the proper container labeling for Soft Chlor Part B.

If product in dip cup becomes visibly dirty, discard contents and replenish with undiluted product. Do not reuse or return any unused product to the original container.

Mix Directions: Measure equal volumes of Soft Chlor Part A and Soft Chlor Part B into clean containers. Mix until uniform in color. Mix only the quantity needed for one milking shift and discard the remainder.

Pre-Milk Dipping: Fill teat dip cup with properly mixed Soft Chlor Part A and Soft Chlor Part B. Before each cow is milked, dip each teat full-length into the teat dip cup containing the product. Wipe teats dry after dipping using single-service towels to avoid contamination of milk.

Post-Milk Dipping: Immediately after each milking, use mixed Soft Chlor Part A and Soft Chlor Part B at full strength. Dip each teat full-length into the teat dip cup containing mixed product. Allow to air dry. Do not wipe. Always use fresh full strength, mixed product. Do not turn cows out in freezing weather until product is completely dry.

PRECAUTION: Soft Chlor Part B is not intended to cure or help the healing of chapped or irritated teats. As with any germicide, irritation or sensitization may occur in sensitive animals. In case of teat irritation or chapping, have the condition examined and, if necessary, treated by a veterinarian.

Consult your Ecolab representative for specific use instructions and recommended dispensing equipment.

OTHER SAFETY INFORMATION

FIRST AID

IN CASE OF EYE CONTACT: Rinse immediately with plenty of water, also under the eyelids, for at least 15 minutes. Remove contact lenses, if present and easy to do. Continue rinsing. Get medical attention immediately.

IN CASE OF SKIN CONTACT: Wash off immediately with plenty of water for at least 15 minutes. Use a mild soap if available. Wash clothing before reuse. Thoroughly clean shoes before reuse. Get medical attention immediately.

IF SWALLOWED: Rinse mouth with water. Do NOT induce vomiting. Never give anything by mouth to an unconscious person. Get medical attention immediately.

IF INHALED: Remove to fresh air. Treat symptomatically. Get medical attention if symptoms occur.

READ SAFETY DATA SHEET (SDS) BEFORE USING THIS PRODUCT

EMERGENCY HEALTH INFORMATION: 1 800 328 0026. If located outside the United States and Canada, call collect 1 651 222 5352 (number is in the US).

PACKAGE LABEL

A&L Laboratories

Soft Chlor™ Part B

Sanitizing Pre/Post Teat Dip

Soft Chlor Part B is formulated to be used as a companion product for Soft Chlor Part A.

An aid in reducing the spread of organisms which may cause mastitis

ACTIVE INGREDIENT:

Stabilized Sodium Salt of Chlorous Acid ........................................................................................ 0.54%

INERT INGREDIENTS:.................................................................................................................... 99.46%

TOTAL:.........................................................................................................................................100.00%

NET CONTENTS: 208 L (55 US GAL)

6301571

Manufactured by

Ecolab Inc. · 370 Wabasha Street N · St Paul MN 55102-1390 USA · tel: 1 800 392 3392

© 2015 Ecolab USA Inc. · All rights reserved

Made in United States